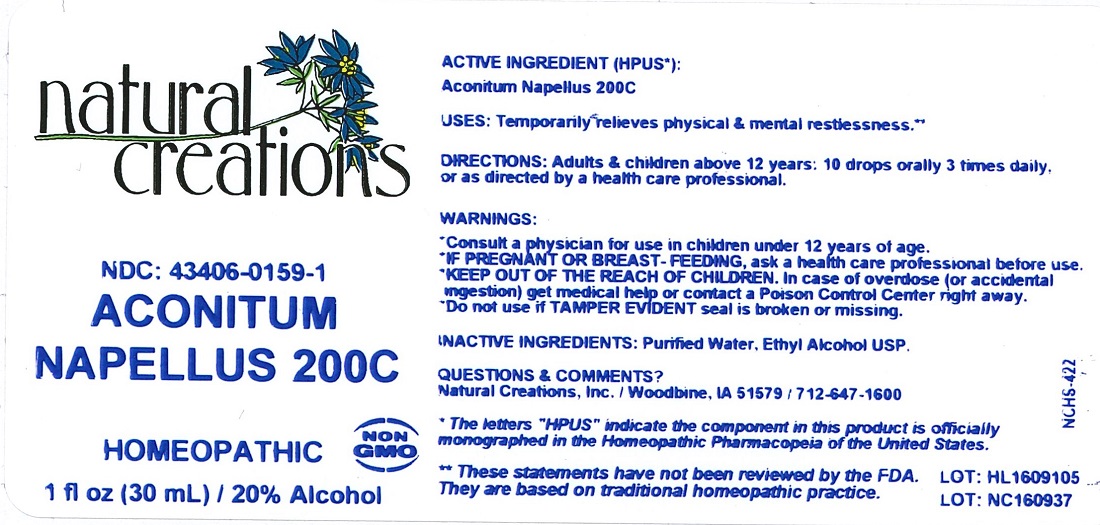 DRUG LABEL: Aconitum Napellus 200C
NDC: 43406-0159 | Form: LIQUID
Manufacturer: Natural Creations, Inc
Category: homeopathic | Type: HUMAN OTC DRUG LABEL
Date: 20220214

ACTIVE INGREDIENTS: ACONITUM NAPELLUS 200 [hp_C]/1 mL
INACTIVE INGREDIENTS: WATER; ALCOHOL

Aconitum Napellus 200C

ACTIVE INGREDIENT (HPUS*): Aconitum Napellus 200C

INDICATIONS AND USAGE

USES: Temporarily relieves physical & mental restlessness.**

PURPOSE

USES: Temporarily relieves physical & mental restlessness.**

DOSAGE AND ADMINISTRATION

DIRECTIONS: Adults & children above 12 years: 10 drops orally 3 times daily, or as directed by a health care professional.

KEEP OUT OF REACH OF CHILDREN

KEEP OUT OF THE REACH OF CHILDREN. In case of overdose (or accidental ingestion) get medical help or contact a Poison Control Center right away.

WARNINGS:

- Consult a physician for use in children under 12 years of age.
- IF PREGNANT OR BREAST-FEEDING, ask a health care professional before use.
- KEEP OUT OF THE REACH OF CHILDREN. In case of overdose (or accidental ingestion) get medical help or contact a Poison Control Center right away.
- Do not use if TAMPER EVIDENT seal is broken or missing.

INACTIVE INGREDIENTS: Purified Water, Ethyl Alcohol USP.

QUESTIONS & COMMENTS?

Natural Creations, Inc. / Woodbine, IA 51579 / 712-647-1600

REFERENCES

*The letters "HPUS" indicate the component in this product is ofiicially monographed in the Homeopathic Pharmacopeia of the United States.

**These statements have not been reviewed by the FDA. They are based on traditional homeopathic practice.

PACKAGE LABEL

NDC: 43406-0159-1

Aconitum Napellus 200C

HOMEOPATHIC

1 fl oz (30mL) / 20% Alcohol